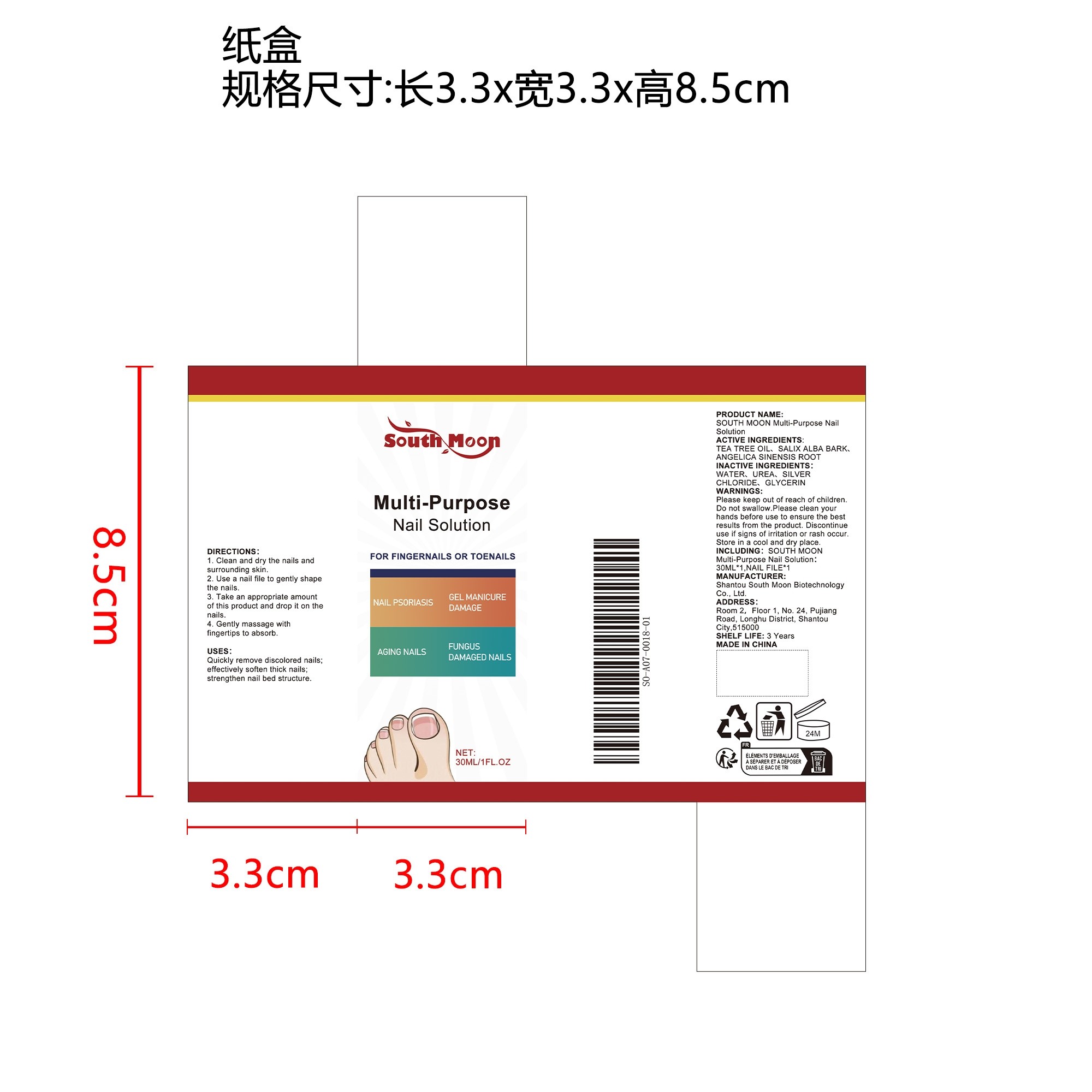 DRUG LABEL: SOUTH MOON Multi-Purpose Nail Solution
NDC: 84983-008 | Form: LIQUID
Manufacturer: Shantou South Moon Biotechnology Co., Ltd.
Category: otc | Type: HUMAN OTC DRUG LABEL
Date: 20251127

ACTIVE INGREDIENTS: ANGELICA SINENSIS ROOT 0.006 mg/30 mg; SALIX ALBA BARK 0.006 mg/30 mg; TEA TREE OIL 0.006 mg/30 mg
INACTIVE INGREDIENTS: WATER 27.876 mg/30 mg; GLYCERIN 0.006 mg/30 mg; SILVER CHLORIDE 0.6 mg/30 mg; UREA 1.5 mg/30 mg

ACTIVE INGREDIENT

TEA TREE OIL、SALIX ALBA BARK、ANGELICA SINENSIS ROOT

WHEN USING

1. Clean and dry the nails and surrounding skin.

2. Use a nail file to gently shape the nails.

3. Take an appropriate amount of this product and drop it on the nails.

4. Gently massage with fingertips to absorb.

PURPOSE

1. Highly effective care, gentle use.

2. Precise penetration, improved appearance.

3. Strengthen nail health, nourish and moisturize.

4. Gentle formula, suitable for sensitive skin.

STOP USE

Discontinue use if signs of irritation or rash occur.

DO NOT USE

Discontinue use if signs of irritation or rash occur.

KEEP OUT OF REACH OF CHILDREN

Please keep out of reach of children. Do not swallow.

STORAGE AND HANDLING

Store in a cool and dry place.

WARNINGS

Please keep out of reach of children. Do not swallow.Please clean your hands before use to ensure the best results from the product. Discontinue use if signs of irritation or rash occur. Store in a cool and dry place.

INACTIVE INGREDIENT

WATER、UREA、SILVER CHLORIDE、GLYCERIN